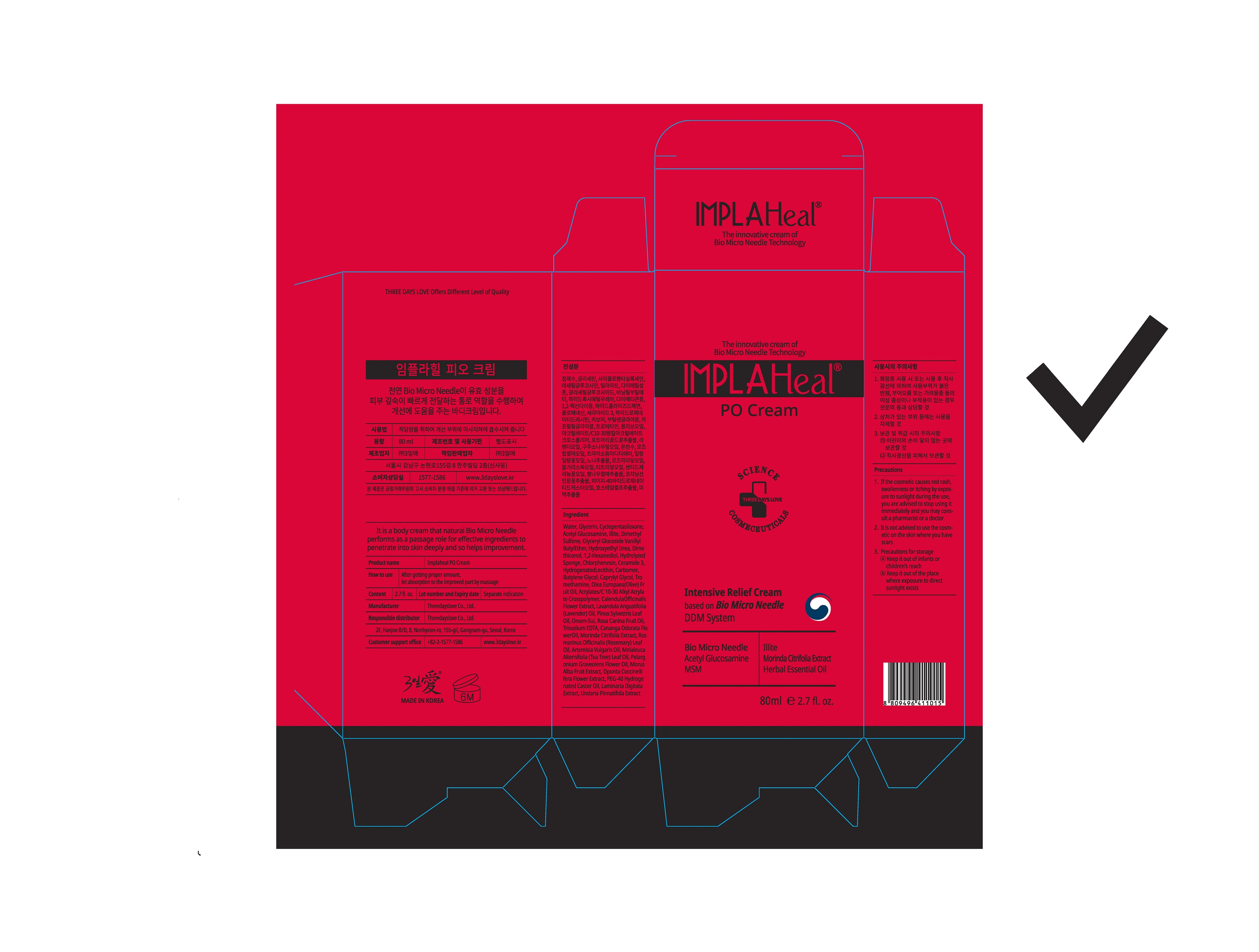 DRUG LABEL: IMPLAHeal P.OCream
NDC: 72368-0007 | Form: CREAM
Manufacturer: Threedayslove Co., Ltd.
Category: otc | Type: HUMAN OTC DRUG LABEL
Date: 20200104

ACTIVE INGREDIENTS: N-ACETYLGLUCOSAMINE 2 g/100 mL; DIMETHYL SULFONE 1 g/100 mL
INACTIVE INGREDIENTS: GLYCERIN; WATER; BUTYLENE GLYCOL

Drug Facts

ACTIVE INGREDIENT

illite, acetyl glucosamine, dimethyl sulfone, hydrolyzed sponge, morinda citrifolia extract,

Olea Europaea (Olive) Fruit Oil
Lavandula Angustifolia (Lavender) Oil
Pinus Sylvestris Leaf Oil
Cananga Odorata Flower Oil
Rosmarinus Officinalis (Rosemary) Leaf Oil
Artemisia Vulgaris Oil
Pelargonium Graveolens Flower Oil
Melaleuca Alternifolia (Tea Tree)Leaf Oil

INACTIVE INGREDIENT

Water
Glycerin
Ceramide 3
Hydrogenated Lecithin
Cyclopentasiloxane
Dimethiconol

etc

PURPOSE

to penetrate into skin deeply and helps improvement

keep out of reach of the children

INDICATIONS AND USAGE

after getting proper amount, let absorption to the improved part by massage

WARNINGS

Warning: 1. Do not use if you have any of following problems during use: ① Rash, red spots, swelling, irritation ② If the application site has any of the above problems due to direct sunlight

2. Precautions for storage and handling ① Close the cap after use ② Keep out of reach of children ③ Do not store under high or low temperature and direct sunlight.

If you continue to use the product, the symptoms may worsen. Stop use and ask a doctor if abnormality occurs.

DOSAGE AND ADMINISTRATION

for external use only